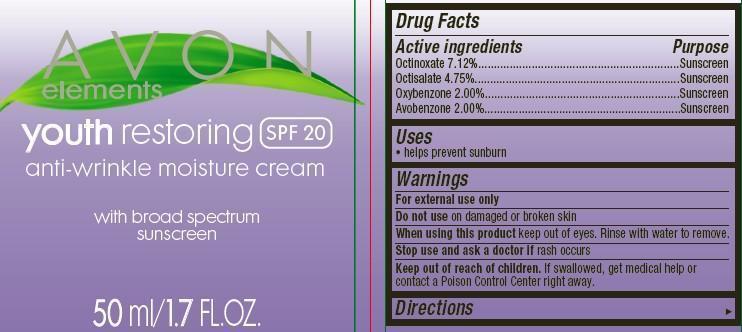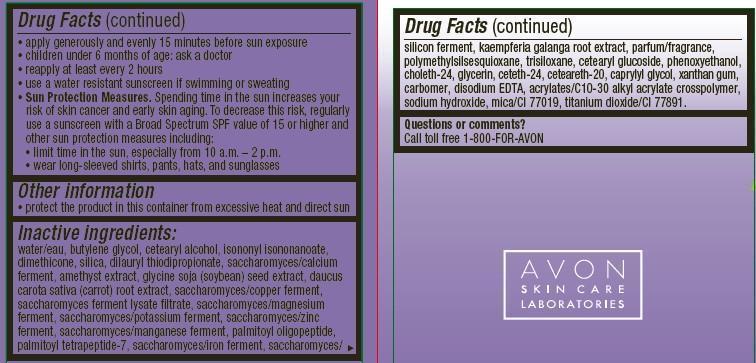 DRUG LABEL: Avon Elements
NDC: 10096-0299 | Form: CREAM
Manufacturer: New Avon LLC
Category: otc | Type: HUMAN OTC DRUG LABEL
Date: 20160219

ACTIVE INGREDIENTS: OCTINOXATE 71.2 mg/1 mL; OCTISALATE 47.5 mg/1 mL; OXYBENZONE 20 mg/1 mL; AVOBENZONE 20 mg/1 mL

Active Ingredients
Octinoxate 7.12%....................................
Octisalate 4.75%.....................................
Oxybenzone 2.00%.................................
Avobenzone 2.00%.................................

Purpose
............... Sunscreen
............... Sunscreen
.............. Sunscreen

.............. Sunscreen

Uses

- helps prevent sunburn

Warnings
For external use only

Do not use on damaged or broken skin

When using this product keep out of eyes. Rinse with water to remove.

Stop use and ask a doctor if rash occurs

Keep out of reach of children. If swallowed, get medical help or contact a Poison Control Center right away.

Directions

- apply generously and evenly 15 minutes before sun exposure
- children under 6 month of age:ask a doctor
- reapply at least every 2 hours
- use a water resistant sunscreen if swimming or sweating
- Sun Protection Measures. Spending time in the sun increases your risk of skin cancer and early skin aging. To decrease this risk, regularly
  use a sunscreen with a Broad Spectrum SPF value of 15 or higher and other sun protection measures including:
  • limit time in the sun, especially from 10 a.m. – 2 p.m.
  • wear long-sleeved shirts, pants, hats, and sunglasses

Other Information

- protect the product in this container from excessive heat and direct sun.

Inactive ingredients:
water/eau, butylene glycol, cetearyl alcohol, isononyl isononanoate, dimethicone, silica, dilauryl thiodipropionate, saccharomyces/calcium
ferment, amethyst extract, glycine soja (soybean) seed extract, daucus carota sativa (carrot) root extract, saccharomyces/copper ferment,
saccharomyces ferment lysate filtrate, saccharomyces/magnesium ferment, saccharomyces/potassium ferment, saccharomyces/zinc
ferment, saccharomyces/manganese ferment, palmitoyl oligopeptide, palmitoyl tetrapeptide-7, saccharomyces/iron ferment, saccharomyces/silicon ferment, kaempferia galanga root extract, parfum/fragrance, polymethylsilsesquioxane, trisiloxane, cetearyl glucoside, phenoxyethanol, choleth-24, glycerin, ceteth-24, ceteareth-20, caprylyl glycol, xanthan gum, carbomer, disodium EDTA, acrylates/C10-30 alkyl acrylate crosspolymer, sodium hydroxide, mica/CI 77019, titanium dioxide/CI 77891.

Questions or comments?
Call toll free 1-800-FOR-AVON